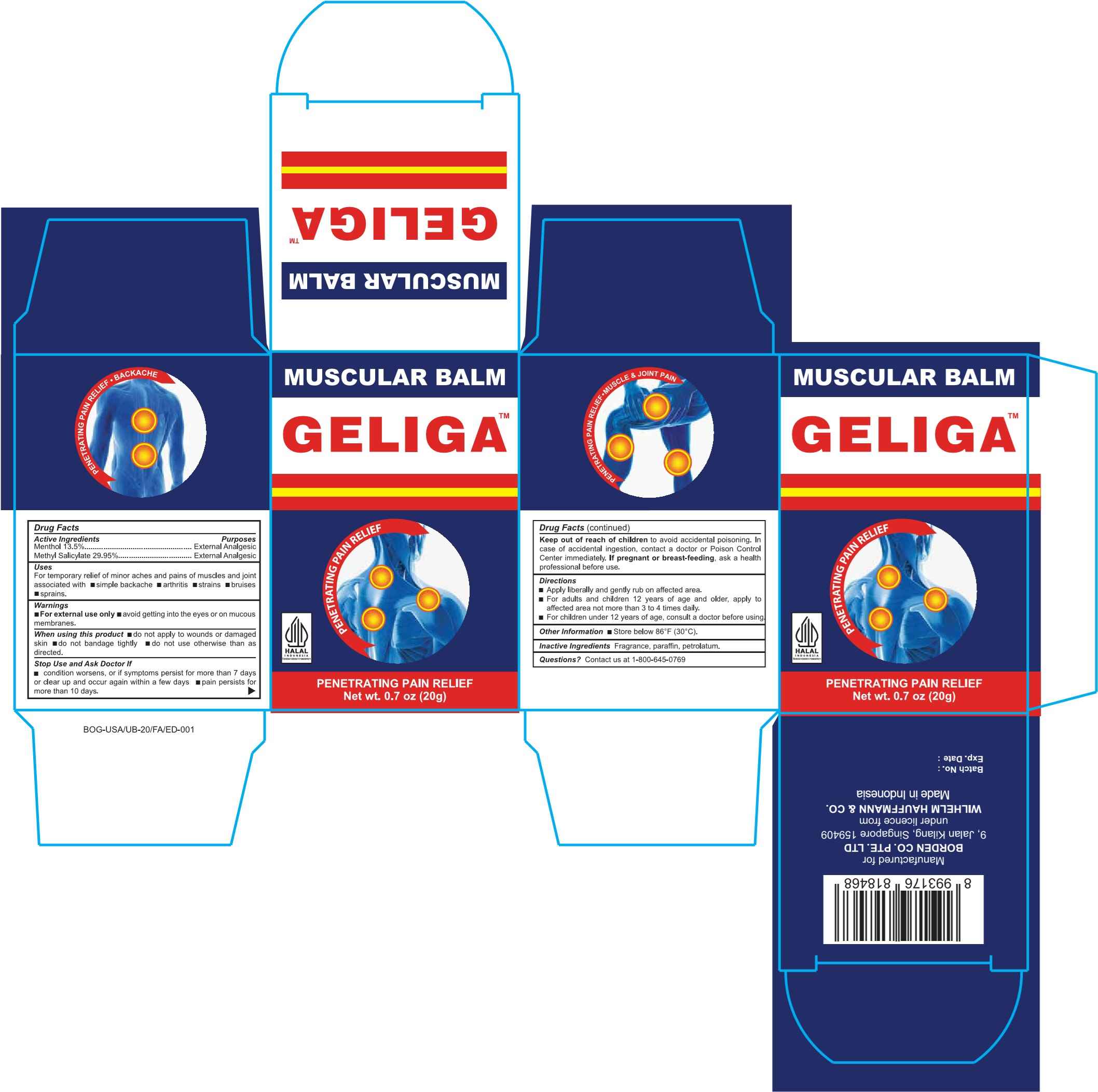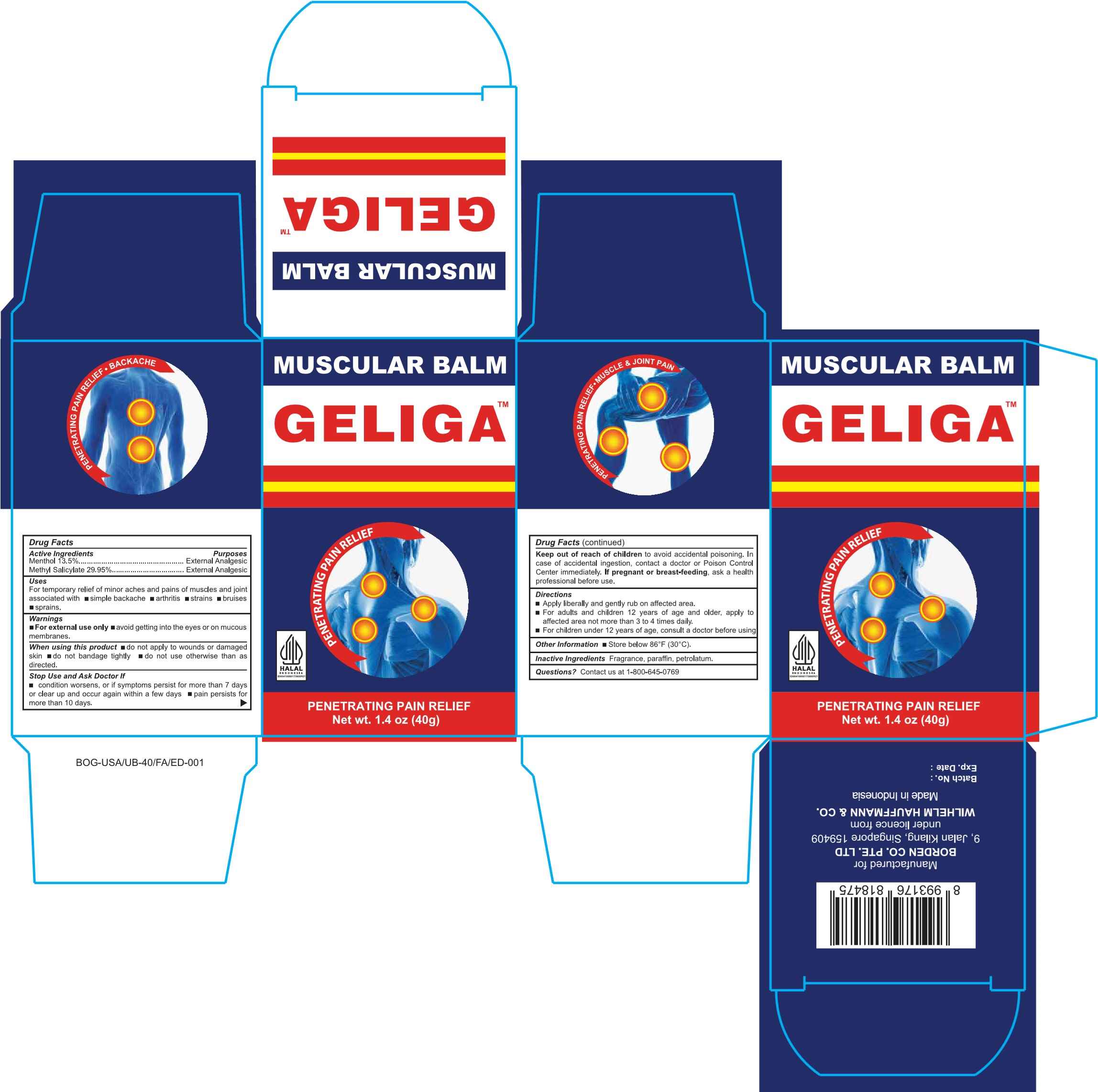 DRUG LABEL: Geliga
NDC: 60954-003 | Form: OINTMENT
Manufacturer: PT. EAGLE INDO PHARMA
Category: otc | Type: HUMAN OTC DRUG LABEL
Date: 20241002

ACTIVE INGREDIENTS: METHYL SALICYLATE 29.95 g/100 g; MENTHOL 13.5 g/100 g
INACTIVE INGREDIENTS: PARAFFIN; PETROLATUM

Geliga Muscular Balm

Active Ingredient(s)

- Menthol 13.5%
- Methyl Salicylate 29.95%

Purpose

External Analgeisc

Uses

For temporary relief of minor aches and pains of muscles and joints associated with simple backache, arthritis, strains, bruises, and sprains.

Warnings

- For external use only
- Avoid getting into eyes or on mucous membranes

When using this product

- Do not apply to wounds or damaged skin.
- Do not bandage tightly.
- Do not use otherwise than as directed.

Stop use and ask a doctor if

- Condition worsens
- Symptoms persist for more than 7 days or clear up and occur again within a few days
- Pain persists for more than 10 days

If pregnant or breast-feeding

If pregnant or beast-feeding, ask a health professional before use.

Keep out of reach of children to avoid accidental poisoning. In case of accidental ingestion, contact a doctor or Poison Control Center immediately

Directions

- Apply liberally and gently rub on affected area.
- For adults and children 12 years and older, apply to affected area not more than 3-4 times daily.
- For children under 12 years of age, consult a doctor before using.

Other information

Store below 86oF (30oC).

Inactive Ingredient(s)

Fragrance, paraffin, petrolatum

Questions

Contact us at 1-800-645-0769

Package Label

20g NDC: 60954-003-20

Package Label

40g NDC: 60954-003-40